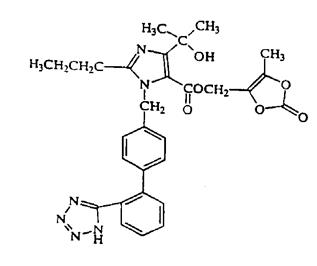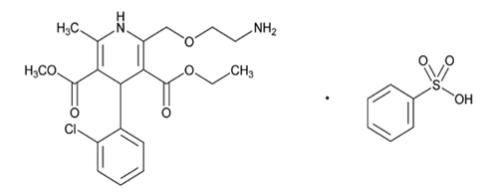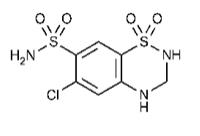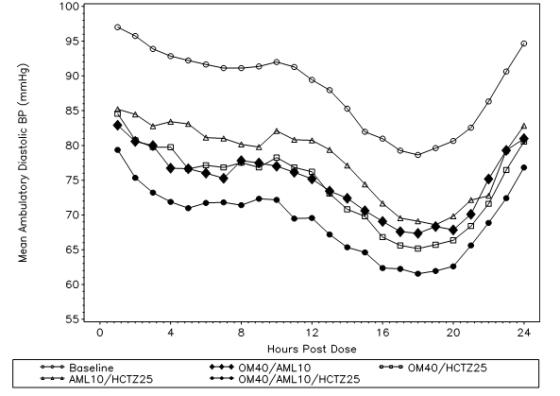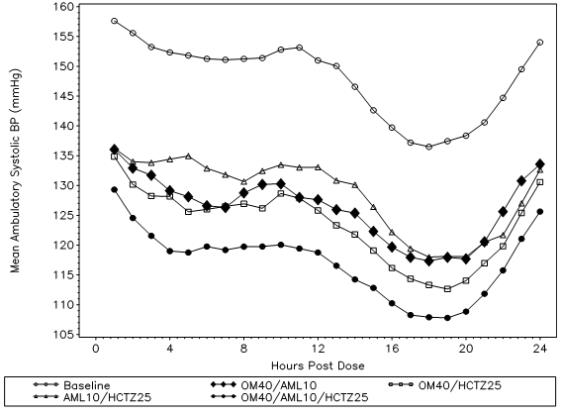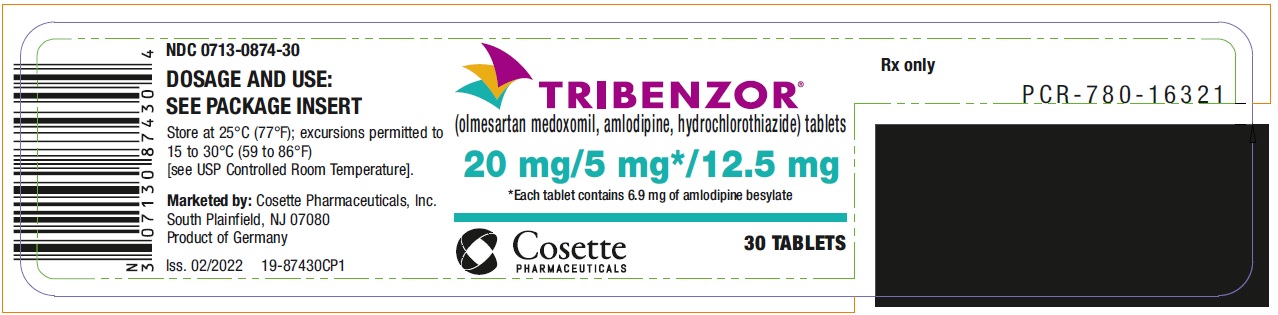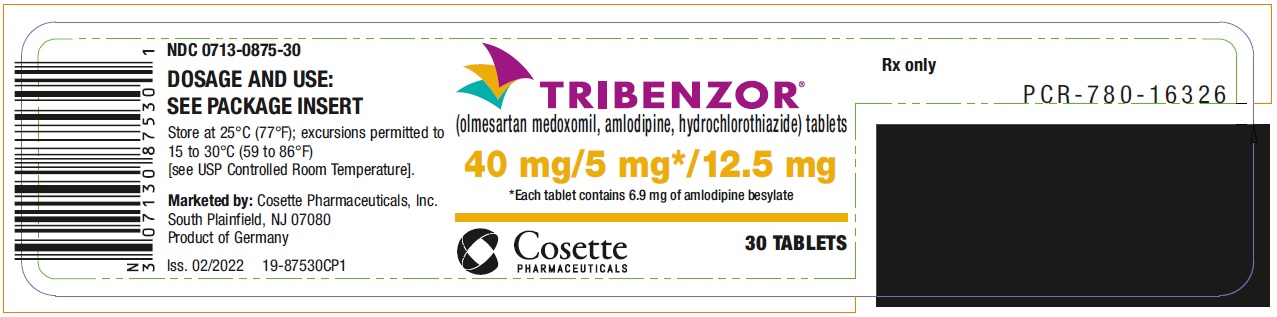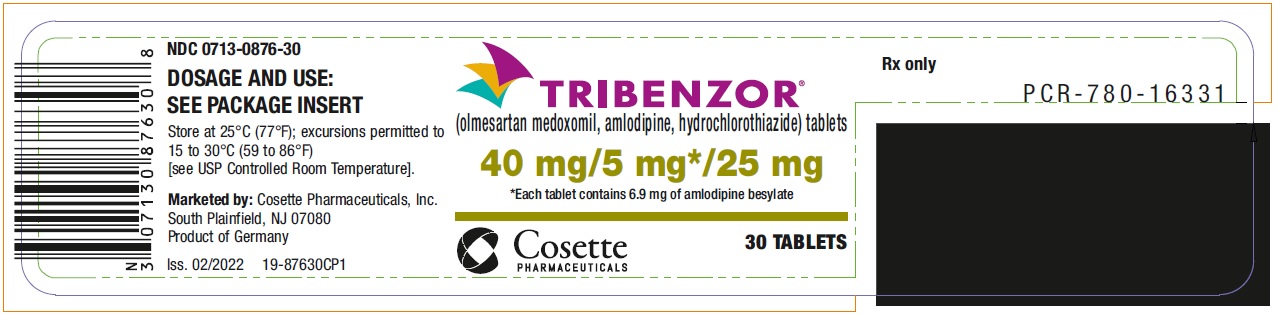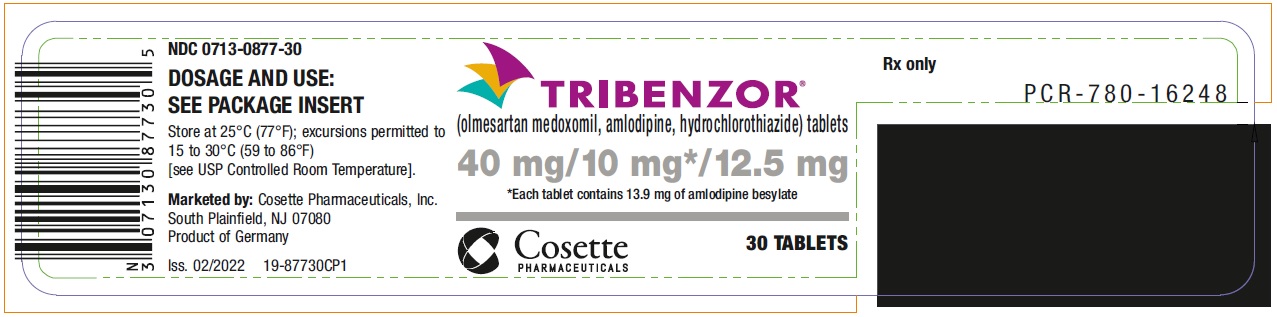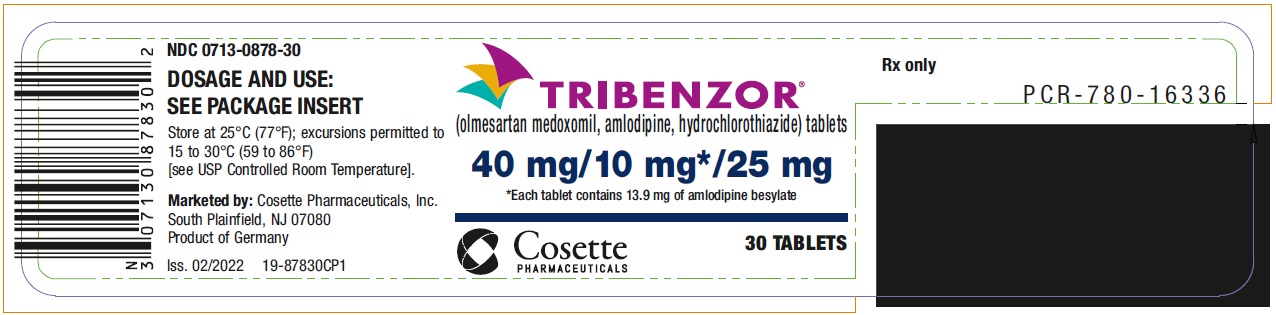 DRUG LABEL: Tribenzor
NDC: 0713-0874 | Form: TABLET, FILM COATED
Manufacturer: Cosette Pharmaceuticals, Inc.
Category: prescription | Type: HUMAN PRESCRIPTION DRUG LABEL
Date: 20230712

ACTIVE INGREDIENTS: OLMESARTAN MEDOXOMIL 20 mg/1 1; AMLODIPINE BESYLATE 5 mg/1 1; HYDROCHLOROTHIAZIDE 12.5 mg/1 1
INACTIVE INGREDIENTS: STARCH, CORN; MICROCRYSTALLINE CELLULOSE; CROSCARMELLOSE SODIUM; MAGNESIUM STEARATE; SILICON DIOXIDE

HIGHLIGHTS OF PRESCRIBING INFORMATION

These highlights do not include all the information needed to use TRIBENZOR safely and effectively. See full prescribing information for TRIBENZOR.
TRIBENZOR (olmesartan medoxomil, amlodipine, hydrochlorothiazide) tablets, for oral use Initial U.S. Approval: 2010

WARNING: FETAL TOXICITY

See full prescribing information for complete boxed warning.

- When pregnancy is detected, discontinue Tribenzor as soon as possible (5.1, 8.1).
- Drugs that act directly on the renin-angiotensin system can cause injury and death to the developing fetus (5.1, 8.1).

1 INDICATIONS AND USAGE

Tribenzor is a combination of olmesartan medoxomil, an angiotensin II receptor blocker, amlodipine, a dihydropyridine calcium channel blocker, and hydrochlorothiazide, a thiazide diuretic, indicated for the treatment of hypertension, to lower blood pressure. Lowering blood pressure reduces the risk of fatal and nonfatal cardiovascular events, primarily strokes and myocardial infarctions. (1).

Limitations of Use

Tribenzor is not indicated for initial therapy (1).

2 DOSAGE AND ADMINISTRATION

- Dose once daily. Dosage may be increased after 2 weeks to a maximum dose of 40 /10 /25 mg once daily (2).
- Dose selection should be individualized based on previous therapy (2).

3 DOSAGE FORMS AND STRENGTHS

Tablets: (olmesartan medoxomil/amlodipine/hydrochlorothiazide) 20 /5 /12.5 mg, 40 /5 /12.5 mg, 40 /5 /25 mg, 40 /10 /12.5 mg, 40 /10 /25 mg (3)

4 CONTRAINDICATIONS

- Anuria: Hypersensitivity to sulfonamide-derived drugs (4).
- Do not co-administer aliskiren with Tribenzor in patients with diabetes (4).

5 WARNINGS AND PRECAUTIONS

- Hypotension: Correct volume or salt depletion prior to administration. (5.2).
- Monitor renal function and potassium in susceptible patients
- Increased angina or myocardial infarction with calcium channel blockers may occur upon dosage initiation or increase (5.3).
- Observe for signs of fluid or electrolyte imbalance (5.6).
- Exacerbation or activation of systemic lupus erythematosus (5.8).
- Acute angle-closure glaucoma (5.9).
- Sprue-like enteropathy has been reported. Consider discontinuation of Tribenzor in cases where no other etiology is found (5.10).

6 ADVERSE REACTIONS

Most common adverse reactions (incidence ≥2%) are dizziness, peripheral edema, headache, fatigue, nasopharyngitis, muscle spasms, nausea, upper respiratory tract infection, diarrhea, urinary tract infection, and joint swelling (6.1).

To report SUSPECTED ADVERSE REACTIONS, Cosette Pharmaceuticals, Inc. at 1-800-922-1038 or FDA at 1-800-FDA-1088 or www.fda.gov/medwatch.

7 DRUG INTERACTIONS

Olmesartan medoxomil (7.1):

- Nonsteroidal anti-inflammatory drugs (NSAIDS): May lead to increased risk of renal impairment and loss of antihypertensive effect.
- Dual inhibition of the renin-angiotensin system: Increased risk of renal impairment, hypotension, and hyperkalemia.
- Colesevelam hydrochloride: Consider administering olmesartan at least 4 hours before colesevelam hydrochloride dose.
- Lithium: Increases in serum lithium concentrations and lithium toxicity.

Amlodipine (7.2):

- Limit simvastatin to 20 mg daily when coadministered.
- Increased exposure to cyclosporin and tacrolimus.
- Increased amlodipine exposure when coadministered with CYP3A inhibitors Hydrochlorothiazide (7.3):
- Antidiabetic drugs: Dosage adjustment of antidiabetic may be required.
- Cholestyramine and colestipol: Reduced absorption of thiazides.
- NSAIDs: Can reduce the diuretic, natriuretic, and antihypertensive effects of diuretics.

8 USE IN SPECIFIC POPULATIONS

- Lactation: Breastfeeding is not recommended (8.2).
- Renal Impairment: Avoid use in patients with creatinine clearance ≤30 mL/min (8.7).

FULL PRESCRIBING INFORMATION

WARNING: FETAL TOXICITY

- When pregnancy is detected, discontinue Tribenzor as soon as possible. (5.1, 8.1)
- Drugs that act directly on the renin-angiotensin system (RAS) can cause injury and death to the developing fetus. (5.1, 8.1)

1 INDICATIONS AND USAGE

Tribenzor is indicated for the treatment of hypertension, alone or with other antihypertensive agents, to lower blood pressure. Lowering blood pressure reduces the risk of fatal and nonfatal cardiovascular (CV) events, primarily strokes and myocardial infarctions. These benefits have been seen in controlled trials of antihypertensive drugs from a wide variety of pharmacologic classes including the class to which this drug principally belongs. There are no controlled trials demonstrating risk reduction with Tribenzor.

Control of high blood pressure should be part of comprehensive cardiovascular risk management, including, as appropriate, lipid control, diabetes management, antithrombotic therapy, smoking cessation, exercise, and limited sodium intake. Many patients will require more than one drug to achieve blood pressure goals. For specific advice on goals and management, see published guidelines, such as those of the National High Blood Pressure Education Program’s Joint National Committee on Prevention, Detection, Evaluation, and Treatment of High Blood Pressure (JNC).

Numerous antihypertensive drugs, from a variety of pharmacologic classes and with different mechanisms of action, have been shown in randomized controlled trials to reduce cardiovascular morbidity and mortality, and it can be concluded that it is blood pressure reduction, and not some other pharmacologic property of the drugs, that is largely responsible for those benefits. The largest and most consistent cardiovascular outcome benefit has been a reduction in the risk of stroke, but reductions in myocardial infarction and cardiovascular mortality also have been seen regularly.

Elevated systolic or diastolic pressure causes increased cardiovascular risk, and the absolute risk increase per mmHg is greater at higher blood pressures, so that even modest reductions of severe hypertension can provide substantial benefit. Relative risk reduction from blood pressure reduction is similar across populations with varying absolute risk, so the absolute benefit is greater in patients who are at higher risk independent of their hypertension (for example, patients with diabetes or hyperlipidemia), and such patients would be expected to benefit from more aggressive treatment to a lower blood pressure goal.

Some antihypertensive drugs have smaller blood pressure effects (as monotherapy) in black patients, and many antihypertensive drugs have additional approved indications and effects (e.g., on angina, heart failure, or diabetic kidney disease). These considerations may guide selection of therapy.

Limitations of Use

This fixed combination drug is not indicated for the initial therapy of hypertension .

2 DOSAGE AND ADMINISTRATION

Dose once daily. Dosage may be increased in 2-week intervals, as needed. The maximum recommended dose of Tribenzor is 40/10/25 mg.

Dose selection should be individualized based on previous therapy.

3 DOSAGE FORMS AND STRENGTHS

Tribenzor tablets are available in the following strength combinations:

 | 20/5/12.5 | 40/5/12.5 | 40/5/25 | 40/10/12.5 | 40/10/25
Olmesartan medoxomil (mg) | 20 | 40 | 40 | 40 | 40
Amlodipine equivalent (mg) | 5 | 5 | 5 | 10 | 10
Hydrochlorothiazide (mg) | 12.5 | 12.5 | 25 | 12.5 | 25

4 CONTRAINDICATIONS

Because of the hydrochlorothiazide component, Tribenzor is contraindicated in patients with anuria, hypersensitivity to any component, or hypersensitivity to other sulfonamide-derived drugs.

Do not co-administer aliskiren with Tribenzor in patients with diabetes [See Drug Interactions (7.2)].

5 WARNINGS AND PRECAUTIONS

5.1 Fetal Toxicity

Olmesartan medoxomil.Tribenzor can cause fetal harm when administered to a pregnant woman. Use of drugs that act on the renin-angiotensin system during the second and third trimesters of pregnancy reduces fetal renal function and increases fetal and neonatal morbidity and death. Resulting oligohydramnios can be associated with fetal lung hypoplasia and skeletal deformations. Potential neonatal adverse effects include skull hypoplasia, anuria, hypotension, renal failure, and death. When pregnancy is detected, discontinue Tribenzor as soon as possible [see Use in specific Populations (8.1].

Hydrochlorothiazide.Thiazides cross the placental barrier and appear in cord blood.

Adverse reactions include fetal or neonatal jaundice and thrombocytopenia [see Use in Specific Populations (8.1)].

5.2 Hypotension in Volume- or Salt-Depleted Patients

Olmesartan medoxomil. In patients with an activated renin-angiotensin system, such as volume- and/or salt-depleted patients (e.g., those being treated with high doses of diuretics) symptomatic hypotension may be anticipated after initiation of treatment with olmesartan medoxomil. Initiate treatment with Tribenzor under close medical supervision. If hypotension does occur, place the patient in the supine position and, if necessary, give an intravenous infusion of normal saline. A transient hypotensive response is not a contraindication to further treatment, which usually can be continued without difficulty once the blood pressure has stabilized.

Amlodipine. Symptomatic hypotension is possible, particularly in patients with severe aortic stenosis. Because of the gradual onset of action, acute hypotension is unlikely.

5.3 Increased Angina and/or Myocardial Infarction

Amlodipine.Patients, particularly those with severe obstructive coronary artery disease, may develop increased frequency, duration, or severity of angina or acute myocardial infarction upon starting calcium channel blocker therapy or at the time of dosage increase. The mechanism of this effect has not been elucidated.

5.4 Impaired Renal Function

Tribenzor.

Impaired renal function was reported in 2.1% of subjects receiving Tribenzor compared to 0.2% to 1.3% of subjects receiving dual combination therapy of olmesartan medoxomil and amlodipine, olmesartan medoxomil and hydrochlorothiazide or amlodipine and hydrochlorothiazide.

If progressive renal impairment becomes evident consider withholding or discontinuing Tribenzor.

Olmesartan medoxomil. Changes in renal function occur in some individuals treated with olmesartan medoxomil as a consequence of inhibiting the renin-angiotensin-aldosterone system. In patients whose renal function may depend upon the activity of the renin-angiotensin-aldosterone system (e.g., patients with severe congestive heart failure), treatment with ACE inhibitors and angiotensin receptor antagonists has been associated with oliguria or progressive azotemia and (rarely) with acute renal failure and/or death. Similar effects may occur in patients treated with Tribenzor due to the olmesartan medoxomil component [see Drug Interactions (7.2) and Clinical Pharmacology (12.3)].

In studies of ACE inhibitors in patients with unilateral or bilateral renal artery stenosis, increases in serum creatinine or blood urea nitrogen (BUN) have been reported. There has been no long-term use of olmesartan medoxomil in patients with unilateral or bilateral renal artery stenosis, but similar effects would be expected with Tribenzor because of the olmesartan medoxomil component.

Hydrochlorothiazide.Thiazides may precipitate azotemia in patients with renal disease. Cumulative effects of the drug may develop in patients with impaired renal function.

5.5 Patients with Hepatic Impairment

Amlodipine. Since amlodipine is extensively metabolized by the liver and the plasma elimination half-life (t1/2) is 56 hours in patients with severely impaired hepatic function, titrate slowly when administering to patients with severe hepatic impairment.

5.6 Electrolyte and Metabolic Imbalances

Tribenzor contains hydrochlorothiazide which can cause hypokalemia, hyponatremia and hypomagnesemia. Hypomagnesemia can result in hypokalemia which may be difficult to treat despite potassium repletion. Tribenzor also contains olmesartan, a drug that affects the RAS. Drugs that inhibit the RAS can also cause hyperkalemia.

Hydrochlorothiazide may alter glucose tolerance and raise serum levels of cholesterol and triglycerides.

Hyperuricemia may occur or frank gout may be precipitated in patients receiving thiazide therapy.

Hydrochlorothiazide decreases urinary calcium excretion and may cause elevations of serum calcium. Monitor calcium levels.

5.7 Postsympathectomy Patients

The antihypertensive effects of the drug may be enhanced in the post-sympathectomy patient.

5.8 Systemic Lupus Erythematosus

Hydrochlorothiazide. Thiazide diuretics have been reported to cause exacerbation or activation of systemic lupus erythematosus.

5.9 Acute Myopia and Secondary Angle-Closure Glaucoma

Hydrochlorothiazide, a sulfonamide, can cause an idiosyncratic reaction, resulting in acute transient myopia and acute angle-closure glaucoma. Symptoms include acute onset of decreased visual acuity or ocular pain and typically occur within hours to weeks of drug initiation. Untreated acute angle-closure glaucoma can lead to permanent vision loss. The primary treatment is to discontinue hydrochlorothiazide as rapidly as possible. Prompt medical or surgical treatments may need to be considered if the intraocular pressure remains uncontrolled. Risk factors for developing acute angle-closure glaucoma may include a history of sulfonamide or penicillin allergy.

5.10 Sprue-like Enteropathy

Olmesartan medoxomil. Severe, chronic diarrhea with substantial weight loss has been reported in patients taking olmesartan months to years after drug initiation. Intestinal biopsies of patients often demonstrated villous atrophy. If a patient develops these symptoms during treatment with olmesartan, exclude other etiologies. Consider discontinuation of Tribenzor in cases where no other etiology is identified.

6 ADVERSE REACTIONS

6.1 Clinical Trials Experience

Because clinical studies are conducted under widely varying conditions, adverse reaction rates observed in the clinical studies of a drug cannot be directly compared to rates in the clinical studies of another drug and may not reflect the rates observed in practice.

Tribenzor

In the controlled trial of Tribenzor, patients were randomized to Tribenzor (olmesartan medoxomil/amlodipine/hydrochlorothiazide 40/10/25 mg), olmesartan medoxomil/amlodipine 40/10 mg, olmesartan medoxomil/hydrochlorothiazide 40/25 mg, or amlodipine/hydrochlorothiazide 10/25 mg. Subjects who received triple combination therapy were treated between two and four weeks with one of the three dual combination therapies. Safety data from this study were obtained in 574 patients with hypertension who received Tribenzor for 8 weeks.

The frequency of adverse reactions was similar between men and women, patients <65 years of age and patients ≥65 years of age, patients with and without diabetes, and Black and non-Black patients. Discontinuations because of adverse events occurred in 4% of patients treated with Tribenzor 40/10/25 mg compared to 1% of patients treated with olmesartan medoxomil/amlodipine 40/10 mg, 2% of patients treated with olmesartan medoxomil/hydrochlorothiazide 40/25 mg, and 2% of patients treated with amlodipine/hydrochlorothiazide 10/25 mg. The most common reason for discontinuation with Tribenzor was dizziness (1%).

Dizziness was one of the most frequently reported adverse reactions with incidence of 1.4% to 3.6% in subjects continuing on dual combination therapy compared to 5.8% to 8.9% in subjects who switched to Tribenzor.

The other most frequent adverse reactions that occurred in at least 2% of subjects are presented in the table below:

Table 1
Adverse Reaction | OM40/ AML10/ HCTZ25 mg (N = 574) n (%) | OM40/ AML10 mg (N = 596) n (%) | OM40/ HCTZ25mg (N = 580) n (%) | AML10/ HCTZ25 mg (N = 552) n (%)
Edema peripheral | 44 (7.7) | 42 (7.0) | 6 (1.0) | 46 (8.3)
Headache | 37 (6.4) | 42 (7.0) | 38 (6.6) | 33 (6.0)
Fatigue | 24 (4.2) | 34 (5.7) | 31 (5.3) | 36 (6.5)
Nasopharyngitis | 20 (3.5) | 11 (1.8) | 20 (3.4) | 16 (2.9)
Muscle spasms | 18 (3.1) | 12 (2.0) | 14 (2.4) | 13 (2.4)
Nausea | 17 (3.0) | 12 (2.0) | 22 (3.8) | 12 (2.2)
Upper respiratory tract infection | 16 (2.8) | 26 (4.4) | 18 (3.1) | 14 (2.5)
Diarrhea | 15 (2.6) | 14 (2.3) | 12 (2.1) | 9 (1.6)
Urinary tract infection | 14 (2.4) | 8 (1.3) | 6 (1.0) | 7 (1.3)
Joint swelling | 12 (2.1) | 17 (2.9) | 2 (0.3) | 16 (2.9)

Syncope was reported by 1% of Tribenzor subjects compared to 0.5% or less for the other treatment groups.

Olmesartan medoxomil

Olmesartan medoxomil has been evaluated for safety in more than 3825 patients/subjects, including more than 3275 patients treated for hypertension in controlled trials. This experience included about 900 patients treated for at least 6 months and more than 525 treated for at least 1 year. Treatment with olmesartan medoxomil was well tolerated, with an incidence of adverse reactions similar to that seen with placebo. Adverse reactions were generally mild, transient, and without relationship to the dose of olmesartan medoxomil.

Amlodipine

Amlodipine has been evaluated for safety in more than 11,000 patients in U.S. and foreign clinical trials.

6.2 Post-Marketing Experience

The following adverse reactions have been identified during post-approval use of the individual components of Tribenzor. Because these reactions are reported voluntarily from a population of uncertain size, it is not always possible to reliably estimate their frequency or establish a causal relationship to drug exposure.

Olmesartan medoxomil.The following adverse reactions have been reported in post-marketing experience:

Body as a Whole:asthenia, angioedema, anaphylactic reactions, peripheral edema

Gastrointestinal:vomiting, diarrhea, sprue-like enteropathy [see Warnings and Precautions (5.10)]

Metabolic and Nutritional Disorders:hyperkalemia

Musculoskeletal:rhabdomyolysis

Urogenital System:acute renal failure, increased blood creatinine

Skin and Appendages:alopecia, pruritus, urticaria

Data from one controlled trial and an epidemiologic study have suggested that high-dose olmesartan may increase cardiovascular (CV) risk in diabetic patients, but the overall data are not conclusive. The randomized, placebo-controlled, double-blind ROADMAP trial (Randomized Olmesartan And Diabetes MicroAlbuminuria Prevention trial, n=4447) examined the use of olmesartan, 40 mg daily, vs. placebo in patients with type 2 diabetes mellitus, normoalbuminuria, and at least one additional risk factor for CV disease. The trial met its primary endpoint, delayed onset of microalbuminuria, but olmesartan had no beneficial effect on decline in glomerular filtration rate (GFR). There was a finding of increased CV mortality (adjudicated sudden cardiac death, fatal myocardial infarction, fatal stroke, revascularization death) in the olmesartan group compared to the placebo group (15 olmesartan vs. 3 placebo, HR 4.9, 95% confidence interval [CI], 1.4, 17), but the risk of non-fatal myocardial infarction was lower with olmesartan (HR 0.64, 95% CI 0.35, 1.18).

The epidemiologic study included patients 65 years and older with overall exposure of > 300,000 patient-years. In the sub-group of diabetic patients receiving high-dose olmesartan (40 mg/d) for > 6 months, there appeared to be an increased risk of death (HR 2.0, 95% CI 1.1, 3.8) compared to similar patients taking other angiotensin receptor blockers. In contrast, high-dose olmesartan use in non-diabetic patients appeared to be associated with a decreased risk of death (HR 0.46, 95% CI 0.24, 0.86) compared to similar patients taking other angiotensin receptor blockers. No differences were observed between the groups receiving lower doses of olmesartan compared to other angiotensin blockers or those receiving therapy for < 6 months.

Overall, these data raise a concern of a possible increased CV risk associated with the use of high-dose olmesartan in diabetic patients. There are, however, concerns with the credibility of the finding of increased CV risk, notably the observation in the large epidemiologic study for a survival benefit in non-diabetics of a magnitude similar to the adverse finding in diabetics.

Amlodipine.The following post-marketing event has been reported infrequently where a causal relationship is uncertain: gynecomastia. In post-marketing experience, jaundice and hepatic enzyme elevations (mostly consistent with cholestasis or hepatitis), in some cases severe enough to require hospitalization, have been reported in association with use of amlodipine. Postmarketing reporting has also revealed a possible association between extrapyramidal disorder and amlodipine.

Hydrochlorothiazide.

Non-melanoma Skin Cancer

Hydrochlorothiazide is associated with an increased risk of non-melanoma skin cancer. In a study conducted in the Sentinel System, increased risk was predominantly for squamous cell carcinoma (SCC) and in white patients taking large cumulative doses. The increased risk for SCC in the overall population was approximately 1 additional case per 16,000 patients per year, and for white patients taking a cumulative dose of ≥50,000 mg the risk increase was approximately 1 additional SCC case for every 6,700 patients per year.

7 DRUG INTERACTIONS

7.1 Drug Interactions with Olmesartan Medoxomil

Non-Steroidal Anti-Inflammatory Agents including Selective Cyclooxygenase-2 Inhibitors (COX-2 Inhibitors):In patients who are elderly, volume-depleted (including those on diuretic therapy), or with compromised renal function, co-administration of NSAIDs, including selective COX-2 inhibitors, with angiotensin II receptor antagonists, including olmesartan medoxomil, may result in deterioration of renal function, including possible acute renal failure. These effects are usually reversible. Monitor renal function periodically in patients receiving olmesartan medoxomil and NSAID therapy.

The antihypertensive effect of angiotensin II receptor antagonists, including olmesartan medoxomil may be attenuated by NSAIDs including selective COX-2 inhibitors.

Dual Blockade of the Renin-Angiotensin System (RAS):Dual blockade of the RAS with angiotensin receptor blockers, ACE inhibitors, or aliskiren is associated with increased risks of hypotension, hyperkalemia, and changes in renal function (including acute renal failure) compared to monotherapy. Most patients receiving the combination of two RAS inhibitors do not obtain any additional benefit compared to monotherapy. In general, avoid combined use of RAS inhibitors. Closely monitor blood pressure, renal function and electrolytes in patients on Tribenzor and other agents that affect the RAS.

Do not co-administer aliskiren with Tribenzor in patients with diabetes [See Contraindications (4)]. Avoid use of aliskiren with Tribenzor in patients with renal impairment (GFR <60 ml/min).

Use with Colesevelam Hydrochloride:Concurrent administration of bile acid sequestering agent colesevelam hydrochloride reduces the systemic exposure and peak plasma concentration of olmesartan. Administration of olmesartan at least 4 hours prior to colesevelam hydrochloride decreased the drug interaction effect. Consider administering olmesartan at least 4 hours before the colesevelam hydrochloride dose [see Clinical Pharmacology (12.3)].

Lithium:Increases in serum lithium concentrations and lithium toxicity have been reported with concomitant use of olmesartan or thiazide diuretics. Monitor lithium levels in patients receiving Tribenzor and lithium.

7.2 Drug Interactions with Amlodipine

Simvastatin:Co-administration of simvastatin with amlodipine increases the systemic exposure of simvastatin. Limit the dose of simvastatin in patients on amlodipine to 20 mg daily. [see Clinical Pharmacology (12.3)].

Immunosuppressants:Amlodipine may increase the systemic exposure of cyclosporine or tacrolimus when co-administered. Frequent monitoring of trough blood levels of cyclosporine and tacrolimus is recommended and adjust the dose when appropriate [see Clinical Pharmacology (12.3)].

CYP3A Inhibitors:Co-administration of amlodipine with CYP3A inhibitors (moderate and strong) results in increased systemic exposure to amlodipine and may require dose reduction. Monitor for symptoms of hypotension and edema when amlodipine is co-administered with CYP3A inhibitors to determine the need for dose adjustment.

CYP3A Inducers:No information is available on the quantitative effects of CYP3A inducers on amlodipine. Blood pressure should be closely monitored when amlodipine is co-administered with CYP3A inducers.

7.3 Drug Interactions with Hydrochlorothiazide

When administered concurrently the following drugs may interact with thiazide diuretics:

Antidiabetic Drugs (oral agents and insulin): Dosage adjustment of the antidiabetic drug may be required.

Cholestyramine and Colestipol Resins: Absorption of hydrochlorothiazide is impaired in the presence of anionic exchange resins. Single dose of either cholestyramine or colestipol resins bind the hydrochlorothiazide and reduce its absorption from the gastrointestinal tract by up to 85% and 43%, respectively.

Corticosteroids, ACTH: Intensified electrolyte depletion, particularly hypokalemia.

Non-steroidal Anti-inflammatory Drugs: In some patients the administration of a non-steroidal anti-inflammatory agent can reduce the diuretic, natriuretic, and antihypertensive effects of loop, potassium-sparing and thiazide diuretics. Therefore, when hydrochlorothiazide tablets and non-steroidal anti-inflammatory agents are used concomitantly, the patients should be observed closely to determine if the desired effect of the diuretic is obtained.

8 USE IN SPECIFIC POPULATIONS

8.1 Pregnancy

Risk Summary

Tribenzor can cause fetal harm when administered to a pregnant woman. Use of drugs that act on the renin-angiotensin system during the second and third trimesters of pregnancy reduces fetal renal function and increases fetal and neonatal morbidity and death [see Clinical Considerations]. Most epidemiologic studies examining fetal abnormalities after exposure to antihypertensive use in the first trimester have not distinguished drugs affecting the renin-angiotensin system from other antihypertensive agents.

When pregnancy is detected, discontinue Tribenzor as soon as possible. Consider alternative antihypertensive therapy during pregnancy.

The estimated background risk of major birth defects and miscarriage for the indicated population is unknown. All pregnancies have a background risk of birth defect, loss or other adverse outcomes. In the U.S. general population, the estimated background risk of major birth defects and miscarriage in clinically recognized pregnancies is 2%–4% and 15%–20%, respectively.

Clinical Considerations

Disease-Associated Maternal and/or Embryo/Fetal Risk

Hypertension in pregnancy increases the maternal risk for pre-eclampsia, gestational diabetes, premature delivery, and delivery complications (e.g., need for cesarean section and post-partum hemorrhage). Hypertension increases the fetal risk for intrauterine growth restriction and intrauterine death. Pregnant women with hypertension should be carefully monitored and managed accordingly.

Fetal/Neonatal Adverse Reactions

Olmesartan medoxomil

Oligohydramnios in pregnant women who use drugs affecting the renin-angiotensin system in the second and third trimesters of pregnancy can result in the following: reduced fetal renal function leading to anuria and renal failure, fetal lung hypoplasia, skeletal deformations, including skull hypoplasia, hypotension, and death.

Perform serial ultrasound examinations to assess the intra-amniotic environment. Fetal testing may be appropriate, based on the week of gestation. Patients and physicians should be aware, however, that oligohydramnios may not appear until after the fetus has sustained irreversible injury.

Closely observe infants with histories of in uteroexposure to olmesartan for hypotension, oliguria, and hyperkalemia. In neonates with a history of in uteroexposure to olmesartan, if oliguria or hypotension occur, utilize measures to maintain adequate blood pressure and renal perfusion. Exchange transfusions or dialysis may be required as a means of reversing hypotension and supporting renal function [see Use in Specific Populations (8.4)].

Hydrochlorothiazide

Thiazides can cross the placenta, and concentrations reached in the umbilical vein approach those in the maternal plasma. Hydrochlorothiazide, like other diuretics, can cause placental hypoperfusion. It accumulates in the amniotic fluid, with reported concentrations up to 19 times that in umbilical vein plasma. Use of thiazides during pregnancy is associated with a risk of fetal or neonatal jaundice or thrombocytopenia. Since they do not prevent or alter the course of preeclampsia, these drugs should not be used to treat hypertension in pregnant women. The use of HCTZ for other indications (e.g., heart disease) in pregnancy should be avoided.

Data

Animal Data

No reproductive studies have been conducted with the combination of olmesartan medoxomil, amlodipine and hydrochlorothiazide. However, these studies have been conducted for olmesartan medoxomil, amlodipine and hydrochlorothiazide alone, and olmesartan medoxomil and hydrochlorothiazide together.

Olmesartan medoxomil.

No teratogenic effects were observed when olmesartan medoxomil was administered to pregnant rats at oral doses up to 1000 mg/kg/day (240 times the maximum recommended human dose [MRHD] on a mg/m^2basis) or pregnant rabbits at oral doses up to 1 mg/kg/day (half the MRHD on a mg/m^2basis; higher doses could not be evaluated for effects on fetal development as they were lethal to the does). In rats, significant decreases in pup birth weight and weight gain were observed at doses ≥1.6 mg/kg/day, and delays in developmental milestones (delayed separation of ear auricular, eruption of lower incisors, appearance of abdominal hair, descent of testes, and separation of eyelids) and dose-dependent increases in the incidence of dilation of the renal pelvis were observed at doses ≥8 mg/kg/day. The no observed effect dose for developmental toxicity in rats is 0.3 mg/kg/day, about one-tenth the MRHD of 40 mg/day.

Olmesartan medoxomil and Hydrochlorothiazide.

No teratogenic effects were observed when 1.6:1 combinations of olmesartan medoxomil and hydrochlorothiazide were administered to pregnant mice at oral doses up to 1625 mg/kg/day (122 times the MRHD on a mg/m^2basis) or pregnant rats up to 1625 mg/kg/day (243 times the MRHD on a mg/m^2basis) or pregnant rabbits at oral doses up to 1 mg/kg/day (0.3 times the MRHD on a mg/m^2basis). In rats, however, fetal body weights at 1625 mg/kg/day (a toxic, sometimes lethal dose in the dams) were significantly lower than control. The no observed effect dose for developmental toxicity in rats is 162.5 mg/kg/day, about 24 times, on a mg/m^2basis, the MRHD of 40 mg olmesartan medoxomil/25 mg hydrochlorothiazide/day. (Calculations based on a 60 kg patient.)

Amlodipine.

No evidence of teratogenicity or other embryo/fetal toxicity was found when pregnant rats and rabbits were treated orally with amlodipine maleate at doses of up to 10 mg amlodipine/kg/day (respectively about 10 and 20 times the maximum recommended human dose of 10 mg amlodipine on a mg/m^2basis) during their respective periods of major organogenesis (calculations based on a patient weight of 60 kg). However, litter size was significantly decreased (by about 50%), and the number of intrauterine deaths was significantly increased (about 5-fold) in rats receiving amlodipine maleate at a dose equivalent to 10 mg amlodipine/kg/day for 14 days before mating and throughout mating and gestation. Amlodipine maleate has been shown to prolong both the gestational period and the duration of labor in rats at this dose.

Hydrochlorothiazide.

No teratogenic effects were observed when hydrochlorothiazide was administered to mice and rats via gavage at doses up to 3000 and 1000 mg/kg/day, respectively (about 600 and 400 times the MRHD), on gestation days 6 through 15.

8.2 Lactation

Risk Summary

There is limited information regarding the presence Tribenzor in human milk, the effects on the breastfed infant, or the effects on milk production. Amlodipine and hydrochlorothiazide are present in human milk. Olmesartan is present in rat milk [see Data] . Because of the potential for adverse effects on the nursing infant, advise a nursing woman that breastfeeding is not recommended during treatment with Tribenzor.

Data

Presence of olmesartan in milk was observed after a single oral administration of 5 mg/kg [^14C] olmesartan medoxomil to lactating rats.

8.4 Pediatric Use

The safety and effectiveness of Tribenzor in pediatric patients have not been established.

8.5 Geriatric Use

Tribenzor.In a controlled clinical trial, 123 hypertensive patients treated with Tribenzor were ≥65 years of age and 18 patients were ≥75 years of age. No overall differences in the efficacy or safety of Tribenzor were observed in these patient populations; however, greater sensitivity of some older individuals cannot be ruled out. The recommended initial dose of amlodipine in patients ≥ 75 years of age is 2.5 mg, a dose not available with Tribenzor.

8.6 Hepatic Impairment

There are no studies of Tribenzor in patients with hepatic insufficiency, but both amlodipine and olmesartan medoxomil show moderate increases in exposure in patients with severe hepatic impairment. The recommended initial dose of amlodipine in patients with severe hepatic impairment is 2.5 mg, a dose not available with Tribenzor [see Warnings and Precautions (5.5)].

Amlodipine.Amlodipine is extensively metabolized by the liver and the plasma elimination half-life (t½) is 56 hours in patients with severely impaired hepatic function.

Olmesartan medoxomil.Increases in AUC0-∞and peak plasma concentration (Cmax) for olmesartan were observed with moderate hepatic impairment compared to those in matched controls with an increase in AUC of about 60%.

Hydrochlorothiazide. In patients with impaired hepatic function or progressive liver disease, minor alterations of fluid and electrolyte balance may precipitate hepatic coma.

8.7 Renal Impairment

There are no studies of Tribenzor in patients with renal impairment. Avoid use in patients with severe renal impairment (creatinine clearance <30 mL/min).

Olmesartan medoxomil.Patients with renal insufficiency have elevated serum concentrations of olmesartan compared with patients with normal renal function. After repeated dosing, AUC was approximately tripled in patients with severe renal impairment (creatinine clearance <20 mL/min). No initial dosage adjustment is recommended for patients with moderate to marked renal impairment (creatinine clearance <40 mL/min). The pharmacokinetics of olmesartan in patients undergoing hemodialysis has not been studied.

Amlodipine.The pharmacokinetics of amlodipine are not significantly influenced by renal impairment.

Hydrochlorothiazide.Thiazide should be used with caution in patients with severe renal disease. In patients with renal disease, thiazides may precipitate azotemia. Cumulative effects of the drug may develop in patients with impaired renal function.

8.8 Black Patients

Of the total number of patients who received Tribenzor in a randomized trial, 29% (184/627) were black. Tribenzor was effective in lowering both systolic and diastolic blood pressure in black patients (usually a low-renin population) to the same extent as in non-black patients.

10 OVERDOSAGE

There is no information on overdosage with Tribenzor in humans.

Olmesartan medoxomil.Limited data are available related to overdosage in humans. The most likely manifestations of overdosage would be hypotension and tachycardia; bradycardia could be encountered if parasympathetic (vagal) stimulation occurs. If symptomatic hypotension should occur, supportive treatment should be initiated. The dialyzability of olmesartan is unknown.

Amlodipine.Single oral doses of amlodipine maleate equivalent to 40 mg amlodipine/kg and 100 mg amlodipine/kg in mice and rats, respectively, caused deaths. Single oral amlodipine maleate doses equivalent to 4 or more mg amlodipine/kg or higher in dogs (11 or more times the maximum recommended human dose on a mg/m^2basis) caused a marked peripheral vasodilation and hypotension.

Overdosage might be expected to cause excessive peripheral vasodilation with marked hypotension and possibly a reflex tachycardia. In humans, experience with intentional overdosage of amlodipine is limited.

If massive overdose should occur, active cardiac and respiratory monitoring should be instituted. Frequent blood pressure measurements are essential. Should hypotension occur, cardiovascular support including elevation of the extremities and the judicious administration of fluids should be initiated. If hypotension remains unresponsive to these conservative measures, administration of vasopressors (such as phenylephrine) should be considered with attention to circulating volume and urine output. Intravenous calcium gluconate may help to reverse the effects of calcium entry blockade. As amlodipine is highly protein bound, hemodialysis is not likely to be of benefit.

Hydrochlorothiazide.The most common signs and symptoms of overdose observed in humans are those caused by electrolyte depletion (hypokalemia, hypochloremia, hyponatremia) and dehydration resulting from excessive diuresis. If digitalis has also been administered, hypokalemia may accentuate cardiac arrhythmias. The degree to which hydrochlorothiazide is removed by hemodialysis has not been established. The oral LD50of hydrochlorothiazide is greater than 10 g/kg in both mice and rats, more than 1000-fold the highest recommended human dose.

11 DESCRIPTION

Tribenzor provided as a tablet for oral administration, is a fixed combination of olmesartan medoxomil (ARB), amlodipine (CCB), and hydrochlorothiazide (thiazide diuretic).

Olmesartan medoxomil, a prodrug, is hydrolyzed to olmesartan during absorption from the gastrointestinal tract.

The olmesartan medoxomil component of Tribenzor is chemically described as 2,3-dihydroxy-2-butenyl 4-(1-hydroxy-1-methylethyl)-2-propyl-1-[ p-(o-1 H-tetrazol-5-ylphenyl)benzyl]imidazole-5-carboxylate, cyclic 2,3-carbonate. Its empirical formula is C29H30N6O6.

The amlodipine besylate component of Tribenzor is chemically described as 3-ethyl-5-methyl (±)-2-[(2-aminoethoxy)methyl]-4-(2-chlorophenyl)-1,4-dihydro-6-methyl-3,5-pyridinedicarboxylate, monobenzenesulphonate. Its empirical formula is C20H25ClN2O5•C6H6O3S.

The hydrochlorothiazide component of Tribenzor is chemically described as 6-chloro-3,4-dihydro-2 H-1,2,4-benzo-thiazidiazine-7-sulfonamide 1,1-dioxide. Its empirical formula is C7H8ClN3O4S2.

The structural formula for olmesartan medoxomil is:

The structural formula for amlodipine besylate is:

The structural formula for hydrochlorothiazide is:

Tribenzor contains olmesartan medoxomil, a white to light yellowish-white powder or crystalline powder, amlodipine besylate, a white to off-white crystalline powder, and hydrochlorothiazide, a white or practically white, crystalline powder. The molecular weights of olmesartan medoxomil, amlodipine besylate, and hydrochlorothiazide are 558.6, 567.1, and 297.7, respectively. Olmesartan medoxomil is practically insoluble in water and sparingly soluble in methanol. Amlodipine besylate is slightly soluble in water and sparingly soluble in ethanol. Hydrochlorothiazide is slightly soluble in water but freely soluble in sodium hydroxide solution.

Each tablet of Tribenzor also contains the following inactive ingredients: silicified microcrystalline cellulose, pregelatinized starch, croscarmellose sodium, and magnesium stearate. The color coating contains polyvinyl alcohol, macrogol/polyethylene glycol 3350, titanium dioxide, talc, iron oxide yellow (20 /5 /12.5 mg, 40 /5 /12.5 mg, 40 /5 /25 mg, 40 /10 /12.5 mg, and 40 /10 /25 mg tablets), iron oxide red (20 /5 /12.5 mg, 40 /10 /12.5 mg, and 40 /10 /25 mg tablets), and iron oxide black (20 /5 /12.5 mg tablets).

12 CLINICAL PHARMACOLOGY

12.1 Mechanism of Action

The active ingredients of Tribenzor target three separate mechanisms involved in blood pressure regulation. Specifically, amlodipine blocks the contractile effects of calcium on cardiac and vascular smooth muscle cells; olmesartan medoxomil blocks the vasoconstriction and sodium retaining effects of angiotensin II on cardiac, vascular smooth muscle, adrenal and renal cells; and hydrochlorothiazide directly promotes the excretion of sodium and chloride in the kidney leading to reductions in intravascular volume. For a more detailed description of the mechanisms of action for each individual component, see below.

Olmesartan medoxomil.Angiotensin II is formed from angiotensin I in a reaction catalyzed by ACE, kininase II. Angiotensin II is the principal pressor agent of the renin-angiotensin system, with effects that include vasoconstriction, stimulation of synthesis and release of aldosterone, cardiac stimulation, and renal reabsorption of sodium. Olmesartan blocks the vasoconstrictor effects of angiotensin II by selectively blocking the binding of angiotensin II to the AT1 receptor in vascular smooth muscle. Its action is, therefore, independent of the pathways for angiotensin II synthesis.

An AT2receptor is found also in many tissues, but this receptor is not known to be associated with cardiovascular homeostasis. Olmesartan has more than a 12,500-fold greater affinity for the AT1receptor than for the AT2receptor.

Blockade of the renin-angiotensin system with ACE inhibitors, which inhibit the biosynthesis of angiotensin II from angiotensin I, is a mechanism of many drugs used to treat hypertension. Angiotensin-converting enzyme inhibitors also inhibit the degradation of bradykinin, a reaction also catalyzed by ACE. Because olmesartan does not inhibit ACE (kininase II), it does not affect the response to bradykinin. Whether this difference has clinical relevance is not yet known.

Blockade of the angiotensin II receptor inhibits the negative regulatory feedback of angiotensin II on renin secretion, but the resulting increased plasma renin activity and circulating angiotensin II levels do not overcome the effect of olmesartan on blood pressure.

Amlodipine. Amlodipine is a dihydropyridine calcium channel blocker that inhibits the transmembrane influx of calcium ions into vascular smooth muscle and cardiac muscle. Experimental data suggests that amlodipine binds to both dihydropyridine and nonhydropyridine binding sites. The contractile processes of cardiac muscle and vascular smooth muscle are dependent upon the movement of extracellular calcium ions into these cells through specific ion channels. Amlodipine inhibits calcium ion influx across cell membranes selectively, with a greater effect on vascular smooth muscle cells than on cardiac muscle cells. Negative inotropic effects can be detected in vitrobut such effects have not been seen in intact animals at therapeutic doses. Serum calcium concentration is not affected by amlodipine. Within the physiologic pH range, amlodipine is an ionized compound (pKa=8.6), and its kinetic interaction with the calcium channel receptor is characterized by a gradual rate of association and dissociation with the receptor binding site, resulting in a gradual onset of effect.

Amlodipine is a peripheral arterial vasodilator that acts directly on vascular smooth muscle to cause a reduction in peripheral vascular resistance and reduction in blood pressure.

Hydrochlorothiazide.Hydrochlorothiazide is a thiazide diuretic. Thiazides affect the renal tubular mechanisms of electrolyte reabsorption, directly increasing excretion of sodium and chloride in approximately equivalent amounts. Indirectly, the diuretic action of hydrochlorothiazide reduces plasma volume, with consequent increases in plasma renin activity, increases in aldosterone secretion, increases in urinary potassium loss, and decreases in serum potassium. The renin-aldosterone link is mediated by angiotensin II, so co-administration of an angiotensin II receptor antagonist tends to reverse the potassium loss associated with these diuretics.

The mechanism of the antihypertensive effect of thiazides is not fully understood.

12.2 Pharmacodynamics

Tribenzor has been shown to be effective in lowering blood pressure. The three components of Tribenzor (olmesartan medoxomil, amlodipine, and hydrochlorothiazide) lower the blood pressure through complementary mechanisms, each working at a separate site and blocking different effects or pathways. The pharmacodynamics of each individual component is described below.

Olmesartan medoxomil.Olmesartan medoxomil doses of 2.5 to 40 mg inhibit the pressor effects of angiotensin I infusion. The duration of the inhibitory effect was related to dose, with doses of olmesartan medoxomil >40 mg giving >90% inhibition at 24 hours.

Plasma concentrations of angiotensin I and angiotensin II and plasma renin activity (PRA) increase after single and repeated administration of olmesartan medoxomil to healthy subjects and hypertensive patients. Repeated administration of up to 80 mg olmesartan medoxomil had minimal influence on aldosterone levels and no effect on serum potassium.

Amlodipine.Following administration of therapeutic doses to patients with hypertension, amlodipine produces vasodilation resulting in a reduction of supine and standing blood pressures. These decreases in blood pressure are not accompanied by a significant change in heart rate or plasma catecholamine levels with chronic dosing.

With chronic once daily oral administration, antihypertensive effectiveness is maintained for at least 24 hours. Plasma concentrations correlate with effect in both young and elderly patients. The magnitude of reduction in blood pressure with amlodipine is also correlated with the height of pretreatment elevation; thus, individuals with moderate hypertension (diastolic pressure 105-114 mmHg) had about a 50% greater response than patients with mild hypertension (diastolic pressure 90-104 mmHg). Normotensive patients experienced no clinically significant change in blood pressures (+1/-2 mmHg).

In hypertensive patients with normal renal function, therapeutic doses of amlodipine resulted in a decrease in renal vascular resistance and an increase in glomerular filtration rate and effective renal plasma flow without change in filtration fraction or proteinuria.

As with other calcium channel blockers, hemodynamic measurements of cardiac function at rest and during exercise (or pacing) in patients with normal ventricular function treated with amlodipine have generally demonstrated a small increase in cardiac index without significant influence on dP/dt or on left ventricular end diastolic pressure or volume. In hemodynamic studies, amlodipine has not been associated with a negative inotropic effect when administered in the therapeutic dose range to intact animals and man, even when co-administered with beta-blockers to man. Similar findings, however, have been observed in normal or well-compensated patients with heart failure with agents possessing significant negative inotropic effects.

Amlodipine does not change sinoatrial nodal function or atrioventricular conduction in intact animals or man. In clinical studies in which amlodipine was administered in combination with beta-blockers to patients with either hypertension or angina, no adverse effects on electrocardiographic parameters were observed.

Hydrochlorothiazide.After oral administration of hydrochlorothiazide, diuresis begins within 2 hours, peaks in about 4 hours, and lasts about 6 to 12 hours.

Drug Interactions

Alcohol, Barbiturates, or Narcotics:Potentiation of orthostatic hypotension may occur.

Skeletal muscle relaxants, non-depolarizing (e.g., tubocurarine): Possible increased responsiveness to the muscle relaxant.

12.3 Pharmacokinetics

Tribenzor. After oral administration of Tribenzor in normal healthy adults, peak plasma concentrations of olmesartan, amlodipine, and hydrochlorothiazide are reached in about 1.5 to 3 hours, 6 to 8 hours, and 1.5 to 2 hours, respectively. The rate and extent of absorption of olmesartan medoxomil, amlodipine, and hydrochlorothiazide from Tribenzor are the same as when administered as individual dosage forms. Food does not affect the bioavailability of Tribenzor.

Olmesartan medoxomil.Olmesartan medoxomil is rapidly and completely bioactivated by ester hydrolysis to olmesartan during absorption from the gastrointestinal tract. The absolute bioavailability of olmesartan medoxomil is approximately 26%. After oral administration, the Cmaxof olmesartan is reached after 1 to 2 hours. Food does not affect the bioavailability of olmesartan medoxomil.

Amlodipine.After oral administration of therapeutic doses of amlodipine, absorption produces peak plasma concentrations between 6 and 12 hours. Absolute bioavailability is estimated between 64% and 90%.

Hydrochlorothiazide.When plasma levels have been followed for at least 24 hours, the plasma half-life has been observed to vary between 5.6 and 14.8 hours.

Distribution

Olmesartan medoxomil.The volume of distribution of olmesartan is approximately 17 L. Olmesartan is highly bound to plasma proteins (99%) and does not penetrate red blood cells. The protein binding is constant at plasma olmesartan concentrations well above the range achieved with recommended doses.

In rats, olmesartan crossed the blood-brain barrier poorly, if at all. Olmesartan passed across the placental barrier in rats and was distributed to the fetus. Olmesartan was distributed to milk at low levels in rats.

Amlodipine. Ex vivostudies have shown that approximately 93% of the circulating drug is bound to plasma proteins in hypertensive patients. Steady-state plasma levels of amlodipine are reached after 7 to 8 days of consecutive daily dosing.

Hydrochlorothiazide.Hydrochlorothiazide crosses the placental but not the blood-brain barrier and is excreted in breast milk.

Metabolism and Excretion

Olmesartan medoxomil.Following the rapid and complete conversion of olmesartan medoxomil to olmesartan during absorption, there is virtually no further metabolism of olmesartan. Total plasma clearance of olmesartan is 1.3 L/h, with a renal clearance of 0.6 L/h. Approximately 35% to 50% of the absorbed dose is recovered in urine while the remainder is eliminated in feces via the bile.

Olmesartan appears to be eliminated in a biphasic manner with a terminal elimination half-life of approximately 13 hours. Olmesartan shows linear pharmacokinetics following single oral doses of up to 320 mg and multiple oral doses of up to 80 mg. Steady-state levels of olmesartan are achieved within 3 to 5 days and no accumulation in plasma occurs with once-daily dosing.

Amlodipine.Amlodipine is extensively (about 90%) converted to inactive metabolites via hepatic metabolism. Elimination from the plasma is biphasic with a terminal elimination half-life of about 30 to 50 hours. Ten percent of the parent compound and 60% of the metabolites are excreted in the urine.

Hydrochlorothiazide.Hydrochlorothiazide is not metabolized but is eliminated rapidly by the kidney. At least 61% of the oral dose is eliminated unchanged within 24 hours.

Specific Populations

Geriatric Patients

Olmesartan medoxomil.The pharmacokinetics of olmesartan medoxomil were studied in the elderly (≥65 years). Overall, maximum plasma concentrations of olmesartan were similar in young adults and the elderly. Modest accumulation of olmesartan was observed in the elderly with repeated dosing; AUCѕѕ, τwas 33% higher in elderly patients, corresponding to an approximate 30% reduction in CLR.

Amlodipine.Elderly patients have decreased clearance of amlodipine with a resulting increase in AUC of approximately 40% to 60%, and a lower initial dose may be required.

Male and Female Patients

Population pharmacokinetic analysis indicated that gender had no effect on the clearance of olmesartan and amlodipine. Female patients had approximately 20% smaller clearances of hydrochlorothiazide than male patients.

Olmesartan medoxomil.Minor differences were observed in the pharmacokinetics of olmesartan medoxomil in women compared to men. Area under the curve and Cmaxwere 10% to 15% higher in women than in men.

Patients with Renal Impairment

Olmesartan medoxomil.In patients with renal insufficiency, serum concentrations of olmesartan were elevated compared to subjects with normal renal function. After repeated dosing, the AUC was approximately tripled in patients with severe renal impairment (creatinine clearance <20 mL/min). The pharmacokinetics of olmesartan medoxomil in patients undergoing hemodialysis has not been studied.

Amlodipine.The pharmacokinetics of amlodipine are not significantly influenced by renal impairment.

Patients with Hepatic Impairment

Olmesartan medoxomil.Increases in AUC0-∞and Cmaxwere observed in patients with moderate hepatic impairment compared to those in matched controls, with an increase in AUC of about 60%.

Amlodipine.Patients with hepatic insufficiency have decreased clearance of amlodipine with a resulting increase in AUC of approximately 40% to 60%.

Heart Failure

Amlodipine.Patients with heart failure have decreased clearance of amlodipine with a resulting increase in AUC of approximately 40% to 60%.

Drug Interaction Studies

Simvastatin: Co-administration of multiple doses of 10 mg of amlodipine with 80 mg simvastatin resulted in a 77% increase in exposure to simvastatin compared to simvastatin alone. [see Drug Interactions (7.2)].

CYP3A inhibitors: Co-administration of a 180 mg daily dose of diltiazem with 5 mg amlodipine in elderly hypertensive patients resulted in a 60% increase in amlodipine systemic exposure. Erythromycin co-administration in healthy volunteers did not significantly change amlodipine systemic exposure. However, strong inhibitors of CYP3A (e.g., itraconazole, clarithromycin) may increase the plasma concentrations of amlodipine to a greater extent [see Drug Interactions (7.2)].

Cyclosporine:In a prospective study in renal transplant patients, an average 40% increase in trough cyclosporine levels was observed in the presence of amlodipine. [see Drug Interactions (7.2)].

Colesevelam: Concomitant administration of 40 mg olmesartan medoxomil and 3750 mg colesevelam hydrochloride in healthy subjects resulted in 28% reduction in Cmax and 39% reduction in AUC of olmesartan. Lesser effects, 4% and 15% reduction in Cmax and AUC respectively, were observed when olmesartan medoxomil was administered 4 hours prior to colesevelam hydrochloride [see Drug Interactions (7.1)].

Cimetidine:Co-administration of amlodipine with cimetidine did not alter the pharmacokinetics of amlodipine.

Grapefruit juice:Co-administration of 240 mL of grapefruit juice with a single oral dose of amlodipine 10 mg in 20 healthy volunteers had no significant effect on the pharmacokinetics of amlodipine.

Maalox® (antacid):Co-administration of the antacid Maalox ®with a single dose of amlodipine had no significant effect on the pharmacokinetics of amlodipine.

Sildenafil:A single 100 mg dose of sildenafil in subjects with essential hypertension had no effect on the pharmacokinetic parameters of amlodipine. When amlodipine and sildenafil were used in combination, each agent independently exerted its own blood pressure lowering effect.

Atorvastatin:Co-administration of multiple 10 mg doses of amlodipine with 80 mg of atorvastatin resulted in no significant change in the steady state pharmacokinetic parameters of atorvastatin.

Digoxin:Co-administration of amlodipine with digoxin did not change serum digoxin levels or digoxin renal clearance in normal volunteers.

No significant drug interactions were reported in studies in which olmesartan medoxomil was coadministered with digoxin in healthy volunteers.

Ethanol (alcohol):Single and multiple 10 mg doses of amlodipine had no significant effect on the pharmacokinetics of ethanol.

Warfarin:Co-administration of amlodipine with warfarin did not change the warfarin prothrombin response time. No significant drug interactions were reported in studies in which olmesartan medoxomil was coadministered with warfarin in healthy volunteers.

Antacids: The bioavailability of olmesartan medoxomil was not significantly altered by the co-administration of antacids [Al(OH)3/Mg(OH)2].

13 NONCLINICAL TOXICOLOGY

The rationale for no or limited new toxicity from the triple combination of olmesartan medoxomil, amlodipine, and hydrochlorothiazide has already been established on the basis of the safety profile of the individual compounds or the dual combinations. To clarify the toxicological profile for Tribenzor, a 3-month repeated dose toxicity study was conducted in rats, and the results demonstrated that the combined administration of olmesartan medoxomil, amlodipine, and hydrochlorothiazide neither augment any existing toxicities of the individual agents nor induce any new toxicities and there were no toxicologically synergistic effects observed in the study.

13.1 Carcinogenesis, Mutagenesis, Impairment of Fertility

No carcinogenicity, mutagenicity or fertility studies have been conducted with the combination of olmesartan medoxomil, amlodipine and hydrochlorothiazide. However, these studies have been conducted for olmesartan medoxomil, amlodipine and hydrochlorothiazide alone.

Olmesartan medoxomil.Olmesartan was not carcinogenic when administered by dietary administration to rats for up to 2 years. The highest dose tested (2000 mg/kg/day) was, on a mg/m^2basis, about 480 times the MRHD of 40 mg/day. Two carcinogenicity studies conducted in mice, a 6-month gavage study in the p53 knockout mouse and a 6-month dietary administration study in the Hras2 transgenic mouse, at doses of up to 1000 mg/kg/day (on a mg/m^2basis, about 120 times the MRHD of 40 mg/day), revealed no evidence of a carcinogenic effect of olmesartan.

Both olmesartan medoxomil and olmesartan tested negative in the in vitroSyrian hamster embryo cell transformation assay and showed no evidence of genetic toxicity in the Ames (bacterial mutagenicity) test. However, both were shown to induce chromosomal aberrations in cultured cells in vitro(Chinese hamster lung) and tested positive for thymidine kinase mutations in the in vitromouse lymphoma assay. Olmesartan medoxomil tested negative in vivofor mutations in the MutaMouse intestine and kidney and for clastogenicity in mouse bone marrow (micronucleus test) at oral doses of up to 2000 mg/kg (olmesartan not tested).

Fertility of rats was unaffected by administration of olmesartan at dose levels as high as 1000 mg/kg/day (240 times the MRHD of 40 mg/day on a mg/m^2basis) in a study in which dosing was begun 2 (female) or 9 (male) weeks prior to mating. (Calculations based on a 60 kg patient.)

Amlodipine.Rats and mice treated with amlodipine maleate in the diet for up to 2 years, at concentrations calculated to provide daily dosage levels of amlodipine 0.5, 1.25, and 2.5 mg/kg/day showed no evidence of a carcinogenic effect of the drug. For the mouse, the highest dose was, on a mg/m^2basis, similar to the MRHD of amlodipine 10 mg/day. For the rat, the highest dose was, on a mg/m^2basis, about two times the MRHD (calculations based on a 60 kg patient).

Mutagenicity studies conducted with amlodipine maleate revealed no drug related effects at either the gene or chromosome level.

There was no effect on the fertility of rats treated orally with amlodipine maleate (males for 64 days and females for 14 days prior to mating) at doses of amlodipine up to 10 mg/kg/day (about 10 times the MRHD of 10 mg/day on a mg/m^2basis).

Hydrochlorothiazide.Two-year feeding studies in mice and rats conducted under the auspices of the National Toxicology Program (NTP) uncovered no evidence of a carcinogenic potential of hydrochlorothiazide in female mice (at doses of up to approximately 600 mg/kg/day) or in male and female rats (at doses of up to approximately 100 mg/kg/day). These doses in mice and rats are about 117 and 39 times, respectively, the MRHD of 25 mg/day on a mg/m^2basis. (Calculations based on a 60 kg patient.) The NTP, however, found equivocal evidence for hepatocarcinogenicity in male mice.

Hydrochlorothiazide was not genotoxic in vitroin the Ames mutagenicity assay of Salmonella typhimuriumstrains TA 98, TA 100, TA 1535, TA 1537, and TA 1538, or in the Chinese Hamster Ovary (CHO) test for chromosomal aberrations. It was also not genotoxic in vivoin assays using mouse germinal cell chromosomes, Chinese Hamster bone marrow chromosomes, or in Drosophilasex-linked recessive lethal trait gene. Positive test results were obtained in the in vitroCHO Sister Chromatid Exchange (clastogenicity) assay, the Mouse Lymphoma Cell (mutagenicity) assay and the Aspergillus nidulansnondisjunction assay.

Hydrochlorothiazide had no adverse effects on the fertility of mice and rats of either sex in studies wherein these species were exposed, via their diet, to doses of up to 100 and 4 mg/kg, respectively, prior to mating and throughout gestation. These doses in mice and rats are about 19 and 1.5 times, respectively, the MRHD of 25 mg/day on a mg/m^2basis. (Calculations based on a 60 kg patient.)

14 CLINICAL STUDIES

14.1 Tribenzor

The antihypertensive efficacy of Tribenzor was studied in a double-blind, active-controlled study in hypertensive patients. A total of 2492 patients with hypertension (mean baseline blood pressure 169/101 mmHg) received olmesartan medoxomil/amlodipine/hydrochlorothiazide 40/10/25 mg (627 patients), olmesartan medoxomil/amlodipine 40/10 mg (628 patients), olmesartan medoxomil/hydrochlorothiazide 40/25 mg (637 patients), or amlodipine/hydrochlorothiazide 10/25 mg (600 patients). Each subject was randomized to one of the three dual therapy combinations for two to four weeks. Patients were then randomized to continue on the dual therapy they were receiving or to receive triple therapy. A total of 53% of patients were male, 19% were 65 years or older, 67% were white, 30% were black, and 15% were diabetic.

After 8 weeks of treatment, the triple combination therapy produced greater reductions in both systolic and diastolic blood pressures (p< 0.0001) compared to each of the 3 dual combination therapies. The full blood pressure lowering effects were attained within 2 weeks after a change in dose.

The seated blood pressure reductions attributable to the addition of a single high-dose drug to each high-dose dual drug combination are shown in Table 2.

Table 2 Additional blood pressure reductions on high-dose Tribenzor compared to high doses of dual combination drugs
Start on | Adding | BP reduction*
Olmesartan medoxomil 40 / amlodipine 10 mg | HCTZ 25 mg | 8.4/4.5 mmHg
Olmesartan medoxomil 40 / HCTZ 25 mg | Amlodipine 10 mg | 7.6/5.4 mmHg
Amlodipine 10 / HCTZ 25 mg | Olmesartan medoxomil 40 mg | 8.1/5.4 mmHg

*all highly statistically significant.

There were no apparent differences in terms of seated diastolic blood pressure (SeDBP) or seated systolic blood pressure (SeSBP) reductions in black and non-black patients treated with Tribenzor [see Use in Specific Populations (8.8)].

There were no apparent differences in terms of SeDBP or SeSBP reductions in diabetic and non-diabetic patients treated with Tribenzor.

A total of 440 patients participated in the ambulatory blood pressure monitoring portion of the study. Over the 24-hour period, there was a greater reduction in diastolic and systolic ambulatory blood pressure for olmesartan medoxomil/amlodipine/hydrochlorothiazide 40/10/25 mg compared to each of the dual combination therapies (see Figure 1 and Figure 2).

Figure 1: Mean Ambulatory Diastolic Blood Pressure at Endpoint by Treatment and Hour

Figure 2: Mean Ambulatory Systolic Blood Pressure at Endpoint by Treatment and Hour

The blood pressure lowering effects of lower dose strengths of Tribenzor (olmesartan medoxomil/amlodipine/hydrochlorothiazide 20/5/12.5 mg, 40/5/12.5 mg, 40/10/12.5 mg, and 40/5/25 mg) have not been studied.

All of the dose strengths of the triple combination are expected to provide superior blood pressure lowering effects compared to their respective mono and dual combination components. The order of the blood pressure lowering effects among the different dose strengths of Tribenzor (olmesartan medoxomil /amlodipine /hydrochlorothiazide) is expected to be 20/5/12.5 mg < 40/5/12.5 mg < (40/10/12.5 mg ≈ 40/5/25 mg) < 40/10/25 mg.

There are no trials of Tribenzor demonstrating reductions in cardiovascular risk in patients with hypertension, but at least one pharmacologically similar drug has demonstrated such benefits.

16 HOW SUPPLIED/STORAGE AND HANDLING

Tribenzor tablets contain olmesartan medoxomil, amlodipine besylate at a dose equivalent to 5 or 10 mg amlodipine, and hydrochlorothiazide in the strengths described below.

Tribenzor tablets are differentiated by tablet color/size and are debossed with an individual product tablet code on one side. Tribenzor tablets are supplied for oral administration in the following strength and package configurations:

Tablet Strength (OM/AML equivalent/HCTZ) | Package Configuration | NDC# | Product Code | Tablet Color
20 /5 /12.5 mg | Bottle of 30 Bottle of 90 10 blisters of 10 | 0713-0874-30 Not available Not available | C51 | Orange white
40 /5 /12.5 mg | Bottle of 30 Bottle of 90 10 blisters of 10 | 0713-0875-30 Not available Not available | C53 | Light yellow
40 /5 /25 mg | Bottle of 30 Bottle of 90 10 blisters of 10 | 0713-0876-30 Not available Not available | C54 | Light yellow
40 /10 /12.5 mg | Bottle of 30 Bottle of 90 10 blisters of 10 | 0713-0877-30 Not available Not available | C55 | Grayish red
40 /10 /25 mg | Bottle of 30 Bottle of 90 10 blisters of 10 | 0713-0878-30 Not available Not available | C57 | Grayish red

Store at 25ºC (77ºF); excursions permitted to 15ºC-30ºC (59ºF-86ºF) [see USP Controlled Room Temperature].

17 PATIENT COUNSELING INFORMATION

Pregnancy: Tell female patients of childbearing age about the consequences of exposure to Tribenzor during pregnancy. Discuss treatment options with women planning to become pregnant. Tell patients to report pregnancies to their physicians as soon as possible [see Warnings and Precautions (5.1)and Use in Specific Populations (8.1)] .

Lactation: Advise nursing women not to breastfeed during treatment with Tribenzor [see Use in Specific Populations (8.2)] .

Symptomatic Hypotension:Advise patients that lightheadedness can occur, especially during the first days of therapy, and that it should be reported to the prescribing physician. Tell patients that if syncope occurs, Tribenzor should be discontinued until the physician has been consulted. Tell patients that inadequate fluid intake, excessive perspiration, diarrhea, or vomiting can lead to an excessive fall in blood pressure, with the same consequences of lightheadedness and possible syncope .

Non-melanoma Skin Cancer:Instruct patients taking hydrochlorothiazide to protect skin from the sun and undergo regular skin cancer screening.

Potassium Supplements:Advise patients not to use potassium supplements or salt substitutes containing potassium without consulting their healthcare provider.

Acute myopia and secondary angle-closure glaucoma: Advise patients to discontinue Tribenzor and seek immediate medical attention if they experience symptoms of acute myopia or secondary angle-closure glaucoma [see Warnings and Precautions (5.9)].

Marketed by Cosette Pharmaceuticals, Inc., South Plainfield, NJ 07080

8-TRIBCP1 Iss. 02/2022

PRINCIPAL DISPLAY PANEL

NDC 0713-0874-30
TRIBENZOR
(olmesartan medoxomil, amlodipine, hydrochlorothiazide) tablets
20 mg/5 mg*/12.5 mg
30 Tablets
Rx only

PRINCIPAL DISPLAY PANEL

NDC 0713-0875-30
TRIBENZOR
(olmesartan medoxomil, amlodipine, hydrochlorothiazide) tablets
40 mg/5 mg*/12.5 mg
30 Tablets
Rx only

PRINCIPAL DISPLAY PANEL

NDC 0713-0876-30
TRIBENZOR
(olmesartan medoxomil, amlodipine, hydrochlorothiazide) tablets
40 mg/5 mg*/25 mg
30 Tablets
Rx only

PRINCIPAL DISPLAY PANEL

NDC 0713-0877-30
TRIBENZOR
(olmesartan medoxomil, amlodipine, hydrochlorothiazide) tablets
40 mg/10 mg*/12.5 mg
30 Tablets
Rx only

PRINCIPAL DISPLAY PANEL

NDC 0713-0878-30
TRIBENZOR
(olmesartan medoxomil, amlodipine, hydrochlorothiazide) tablets
40 mg/10 mg*/25 mg
30 Tablets
Rx only